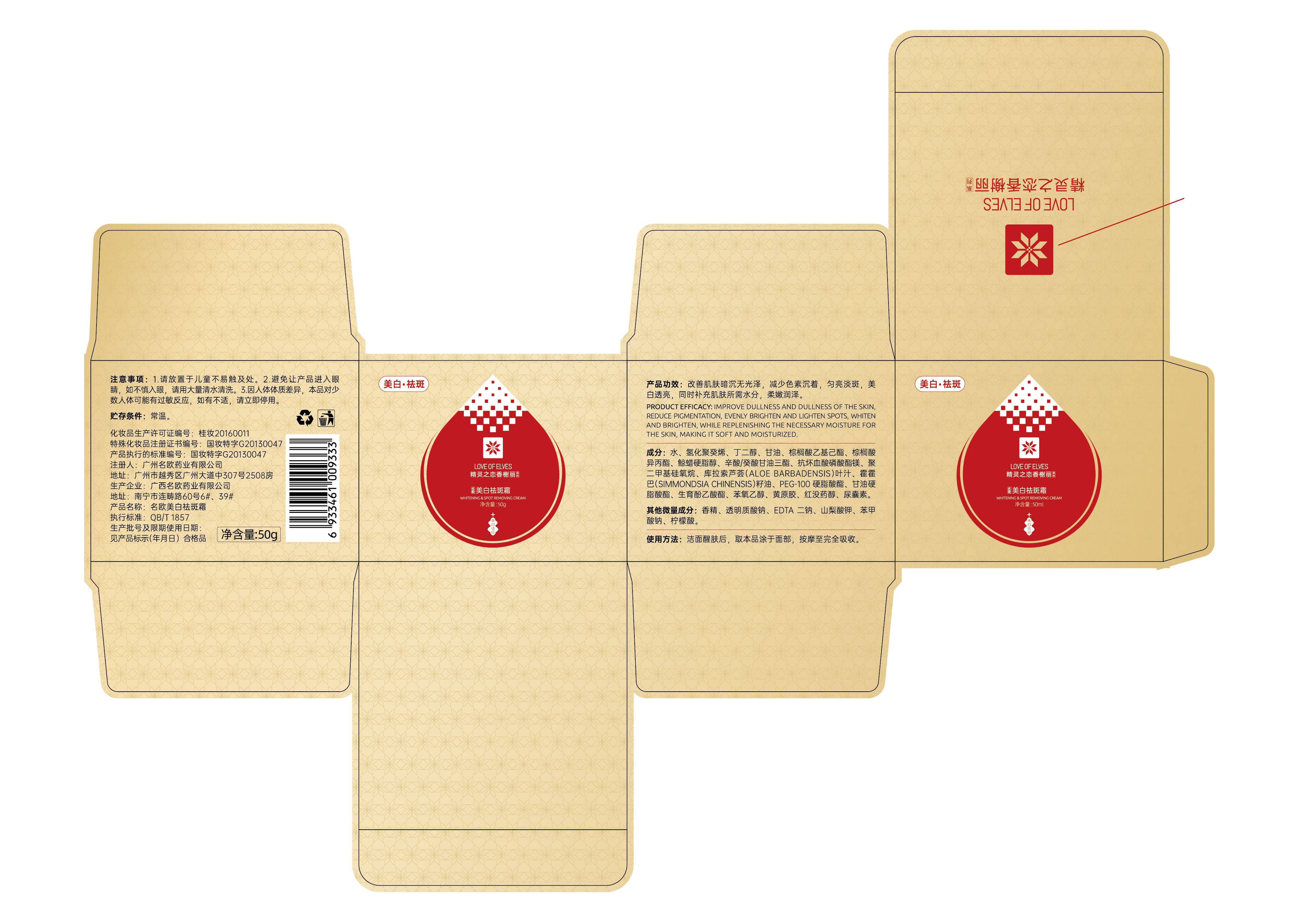 DRUG LABEL: Whitening and anti-freckle cream
NDC: 84778-001 | Form: LOTION
Manufacturer: Guangzhou Yixin Cross-border E-commerce Co., Ltd.
Category: otc | Type: HUMAN OTC DRUG LABEL
Date: 20240925

ACTIVE INGREDIENTS: MAGNESIUM ASCORBYL PHOSPHATE 2 g/2 g
INACTIVE INGREDIENTS: GLYCERIN; ETHYLHEXYL PALMITATE; PEG-100 STEARATE; GLYCERYL MONOSTEARATE; POTASSIUM SORBATE; DIMETHICONE; .ALPHA.-TOCOPHEROL ACETATE; PHENOXYETHANOL; LEVOMENOL; HYALURONATE SODIUM; HYDROGENATED POLYDECENE TYPE I; ISOPROPYL PALMITATE; SODIUM BENZOATE; JOJOBA OIL; EDETATE DISODIUM; WATER; XANTHAN GUM; ALLANTOIN; MEDIUM-CHAIN TRIGLYCERIDES; CETOSTEARYL ALCOHOL; ACONITIC ACID; FRAGRANCE EUCALYPTUS SPEARMINT ORC1601627; ALOE VERA LEAF; BUTYLENE GLYCOL

COMPONENTS

MAGNESIUM ASCORBYL PHOSPHATE 2%

PURPOSE

To help smooth the look of wrinkles, even skin tone

INDICATIONS AND USAGE

Smooth evenly over your cleansed face and neck morning and night.

WARNINGS

For external use only

Do not use on damaged or broken skin

When using this product keep out of eyes. Rinse with water to remove.

Stop use and ask a doctor if rash occurs

Keep out of reach of children.lf swallowed, get medical help or contact a Poison Control Center right away.

DOSAGE AND ADMINISTRATION

For external use only.

Stop use and ask a doctor if rash occurs

Do not use on damaged or broken skin

Keep out of reach of children.lf swallowed, get medical help or contacta Poison Control Center right away.

INACTIVE INGREDIENT

AQUA,HYDROGENATED POLYDECENE,BUTYLENE GLYCOL,GLYCERIN,ETHYLHEXYL PALMITATE,ISOPROPYL PALMITATE,PEG-100 STEARATE,GLYCERYL STEARATE,ALOE BARBADENSIS LEAF JUICE,POTASSIUM SORBATE,SODIUM,BENZOATE,CITRIC ACID,CETEARYL ALCOHOL,DIMETHICONE,CAPRYLIC/CAPRIC TRIGLYCERIDE,SIMMONDSIA CHINENSIS (JOJOBA) SEED OIL,TOCOPHERYL ACETATE,PHENOXYETHANOL,XANTHAN GUM,BISABOLOL,ALLANTOIN,FRAGRANCE,DISODIUM EDTA,SODIUM HYALURONATE